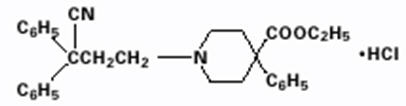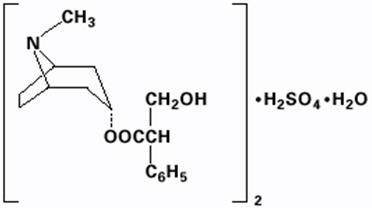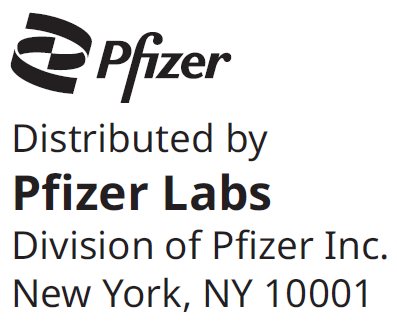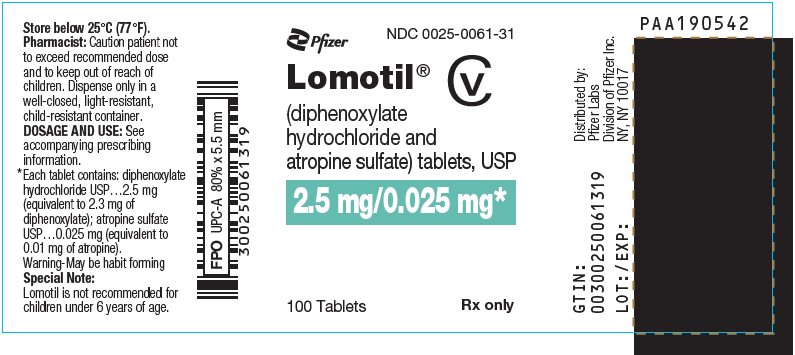 DRUG LABEL: Lomotil
NDC: 0025-0061 | Form: TABLET
Manufacturer: Pfizer Laboratories Div Pfizer Inc
Category: prescription | Type: HUMAN PRESCRIPTION DRUG LABEL
Date: 20260223
DEA Schedule: CV

ACTIVE INGREDIENTS: DIPHENOXYLATE HYDROCHLORIDE 2.5 mg/1 1; ATROPINE SULFATE 0.025 mg/1 1
INACTIVE INGREDIENTS: ACACIA; STARCH, CORN; MAGNESIUM STEARATE; SORBITOL; SUCROSE; TALC

LOMOTIL (diphenoxylate hydrochloride and atropine sulfate tablets), for oral use, C-V

DESCRIPTION

Each Lomotil tablet contains:

2.5 mg of diphenoxylate hydrochloride USP (equivalent to 2.3 mg of diphenoxylate) and 0.025 mg of atropine sulfate USP (equivalent to 0.01 mg of atropine)

Diphenoxylate hydrochloride, an antidiarrheal, is ethyl 1-(3-cyano-3,3-diphenylpropyl)-4-phenylisonipecotate monohydrochloride and has the following structural formula:

Atropine sulfate, an anticholinergic, is endo-(±)-α-(hydroxymethyl) benzeneacetic acid 8-methyl-8-azabicyclo[3.2.1] oct-3-yl ester sulfate (2:1) (salt) monohydrate and has the following structural formula:

A subtherapeutic amount of atropine sulfate is present to discourage deliberate overdosage.

Inactive ingredients of Lomotil tablets include acacia, corn starch, magnesium stearate, sorbitol, sucrose, and talc.

CLINICAL PHARMACOLOGY

Diphenoxylate is rapidly and extensively metabolized in man by ester hydrolysis to diphenoxylic acid (difenoxine), which is biologically active and the major metabolite in the blood. After a 5 mg oral dose of carbon-14 labeled diphenoxylate hydrochloride in ethanolic solution was given to three healthy volunteers, an average of 14% of the drug plus its metabolites was excreted in the urine and 49% in the feces over a four-day period. Urinary excretion of the unmetabolized drug constituted less than 1% of the dose, and diphenoxylic acid plus its glucuronide conjugate constituted about 6% of the dose. In a 16-subject crossover bioavailability study, a linear relationship in the dose range of 2.5 to 10 mg was found between the dose of diphenoxylate hydrochloride (given as Lomotil liquid) and the peak plasma concentration, the area under the plasma concentration-time curve, and the amount of diphenoxylic acid excreted in the urine. In the same study the bioavailability of the tablet compared with an equal dose of the liquid was approximately 90%. The average peak plasma concentration of diphenoxylic acid following ingestion of four 2.5 mg tablets was 163 ng/ml at about 2 hours, and the elimination half-life of diphenoxylic acid was approximately 12 to 14 hours.

In dogs, diphenoxylate hydrochloride has a direct effect on circular smooth muscle of the bowel that conceivably results in segmentation and prolongation of gastrointestinal transit time. The clinical antidiarrheal action of diphenoxylate hydrochloride may thus be a consequence of enhanced segmentation that allows increased contact of the intraluminal contents with the intestinal mucosa.

INDICATIONS AND USAGE

Lomotil is indicated as adjunctive therapy in the management of diarrhea in patients 13 years of age and older.

CONTRAINDICATIONS

Lomotil is contraindicated in:

- Pediatric patients less than 6 years of age due to the risks of respiratory and central nervous system (CNS) depression (see WARNINGS).
- Patients with diarrhea associated with pseudomembranous enterocolitis (Clostridium difficile) or other enterotoxin-producing bacteria due to the risk of gastrointestinal (GI) complications, including sepsis (see WARNINGS).
- Patients with known hypersensitivity to diphenoxylate or atropine.
- Patients with obstructive jaundice.

WARNINGS

Respiratory and/or CNS Depression in Pediatric Patients Less Than 6 Years of Age

Cases of severe respiratory depression and coma, leading to permanent brain damage or death have been reported in patients less than 6 years of age who received Lomotil. Lomotil is contraindicated in patients less than 6 years of age due to these risks (see CONTRAINDICATIONS).

Anticholinergic and Opioid-Toxicities

Toxicities associated with the atropine and diphenoxylate components of Lomotil have been reported. The initial presenting symptoms may be delayed by up to 30 hours due to prolonged gastric emptying time induced by diphenoxylate hydrochloride. Clinical presentations vary in terms of which toxicity (anticholinergic vs. opioid) will present first or predominate; non-specific findings have been reported and include symptoms such as drowsiness (see OVERDOSAGE).

Dehydration and Electrolyte Imbalance

The use of Lomotil should be accompanied by appropriate fluid and electrolyte therapy, when indicated. If severe dehydration or electrolyte imbalance is present, Lomotil should be withheld until appropriate corrective therapy has been initiated. Drug-induced inhibition of peristalsis may result in fluid retention in the intestine, which may further aggravate dehydration and electrolyte imbalance.

Gastrointestinal Complications in Patients with Infectious Diarrhea

Lomotil is contraindicated in patients with diarrhea associated with organisms that penetrate the GI mucosa (toxigenic E. coli, Salmonella, Shigella), and pseudomembranous enterocolitis (Clostridium difficile) associated with broad-spectrum antibiotics (see CONTRAINDICATIONS). Antiperistaltic agents, including Lomotil, slow gastrointestinal motility and may enhance bacterial overgrowth and the release of bacterial exotoxins. Lomotil has been reported to result in serious GI complications in patients with infectious diarrhea, including sepsis, prolonged and/or worsened diarrhea. Prolonged fever and the delay in the resolution of stool pathogens were reported in study of Shigellosis in adults who used Lomotil vs. placebo.

Toxic Megacolon in Patients with Acute Ulcerative Colitis

In some patients with acute ulcerative colitis, agents that inhibit intestinal motility or prolong intestinal transit time have been reported to induce toxic megacolon. Consequently, patients with acute ulcerative colitis should be carefully observed and Lomotil therapy should be discontinued promptly if abdominal distention occurs or if other untoward symptoms develop.

Interaction with Meperidine Hydrocholoride

Since the chemical structure of diphenoxylate hydrochloride is similar to that of meperidine hydrochloride, the concurrent use of Lomotil with monoamine oxidase (MAO) inhibitors may, in theory, precipitate hypertensive crisis.

Hepatorenal Disease

Lomotil should be used with extreme caution in patients with advanced hepatorenal disease and in all patients with abnormal liver function since hepatic coma may be precipitated.

Interaction with CNS Depressants

Diphenoxylate hydrochloride may potentiate the action of other drugs that cause dizziness or drowsiness, including barbiturates, benzodiazepines and other sedatives/hypnotics, anxiolytics, and tranquilizers, muscle relaxants, general anesthetics, antipsychotics, other opioids, and alcohol. Therefore, the patient should be closely observed when any of these are used concomitantly.

PRECAUTIONS

Atropinism

Since a subtherapeutic dose of atropine has been added to Lomotil, consideration should be given to the development of adverse reactions associated with atropine (see WARNINGS). Lomotil has caused atropinism (hyperthermia, tachycardia, urinary retention, flushing, dryness of the skin and mucous membranes) particularly in pediatric patients with Down's syndrome. Lomotil is not indicated for use in pediatric patients (see CONTRAINDICATIONS and WARNINGS). Monitor patients for signs of atropinism.

Information for patients:

Advise patients:

- Accidental ingestion of Lomotil in children, especially in those less than 6 years of age, may result in severe respiratory depression or coma. Instruct patients to take steps to store Lomotil securely and out of reach of children, and to dispose of unused Lomotil (see WARNINGS).
- To take Lomotil at the prescribed dosage. Use of a higher than prescribed dosage may include opioid and/or anticholinergic effects (see OVERDOSAGE). Report to a healthcare facility if they develop anticholinergic symptoms such as hyperthermia, flushing, tachycardia, tachypnea, hypotonia, lethargy, hallucinations, febrile convulsion, dry mouth, mydriasis or opioid symptoms such as progressive CNS and respiratory depression, miosis, seizures, or paralytic ileus.
- Lomotil may produce drowsiness or dizziness. Concomitant use of alcohol or other drugs that also cause CNS depression (e.g., barbiturates, benzodiazepines, opioids, buspirone, antihistamines, and muscle relaxants) may increase this effect. Inform patients not to operate motor vehicles or other dangerous machinery until they are reasonably certain that Lomotil does not affect them adversely.
- To use fluid and electrolyte therapy, if prescribed along with Lomotil, as instructed by their healthcare provider.
- Clinical improvement of diarrhea is usually observed within 48 hours. If clinical improvement is not seen within 10 days, discontinue Lomotil and contact their healthcare provider.

Drug interactions:

Alcohol

Alcohol may increase the CNS depressant effects of Lomotil and may cause drowsiness (see WARNINGS). Avoid concomitant use of Lomotil with alcohol.

Other Drugs that Cause CNS Depression

The concurrent use of Lomotil with other drugs that cause CNS depression (e.g., barbiturates, benzodiazepines, opioids, buspirone, antihistamines, muscle relaxants), may potentiate the effects of Lomotil (see WARNINGS). Either Lomotil or the other interacting drug should be chosen, depending on the importance of the drug to the patient. If CNS-acting drugs cannot be avoided, monitor patients for CNS adverse reactions.

MAO Inhibitors

Diphenoxylate may interact with monoamine oxidase inhibitors (MAOIs) and precipitate a hypertensive crisis. Avoid use of Lomotil in patients who take MAOIs and monitor for signs and symptoms of hypertensive crisis (headache, hyperthermia, hypertension).

Carcinogenesis, mutagenesis, impairment of fertility

No long-term study in animals has been performed to evaluate carcinogenic potential. Diphenoxylate hydrochloride was administered to male and female rats in their diets to provide dose levels of 4 and 20 mg/kg/day throughout a three-litter reproduction study. At 50 times the human dose (20 mg/kg/day), female weight gain was reduced and there was a marked effect on fertility as only 4 of 27 females became pregnant in three test breedings. The relevance of this finding to usage of Lomotil in humans is unknown.

Pregnancy

Diphenoxylate hydrochloride has been shown to have an effect on fertility in rats when given in doses 50 times the human dose (see above discussion). Other findings in this study include a decrease in maternal weight gain of 30% at 20 mg/kg/day and of 10% at 4 mg/kg/day. At 10 times the human dose (4 mg/kg/day), average litter size was slightly reduced.

Teratology studies were conducted in rats, rabbits, and mice with diphenoxylate hydrochloride at oral doses of 0.4 to 20 mg/kg/day. Due to experimental design and small numbers of litters, embryotoxic, fetotoxic, or teratogenic effects cannot be adequately assessed. However, examination of the available fetuses did not reveal any indication of teratogenicity.

There are no adequate and well-controlled studies in pregnant women. Lomotil should be used during pregnancy only if the anticipated benefit justifies the potential risk to the fetus.

Nursing mothers

Caution should be exercised when Lomotil is administered to a nursing woman, since the physicochemical characteristics of the major metabolite, diphenoxylic acid, are such that it may be excreted in breast milk and since it is known that atropine is excreted in breast milk.

Pediatric use

The safety and effectiveness of Lomotil have been established in pediatric patients 13 years of age and older as adjunctive therapy in the management of diarrhea. The safety and effectiveness of Lomotil have not been established in pediatric patients less than 13 years of age.

Lomotil is contraindicated in pediatric patients less than 6 years of age due to the risks of severe respiratory depression and coma, possibly resulting in permanent brain damage or death (see CONTRAINDICATIONS).

Lomotil has caused atropinism, particularly in pediatric patients with Down's syndrome (see PRECAUTIONS).

In case of accidental ingestion of Lomotil by pediatric patients, see OVERDOSAGE for recommended treatment.

ADVERSE REACTIONS

The following serious adverse reactions are described elsewhere in labeling:

- Respiratory and/or CNS depression (see WARNINGS)
- Anticholinergic and opioid-toxicities, including atroponism (see WARNINGS and PRECAUTIONS)
- Dehydration and electrolyte imbalance (see WARNINGS)
- GI Complications in patients with infectious diarrhea (see WARNINGS)
- Toxic megacolon in patients with acute ulcerative colitis (see WARNINGS)

At therapeutic doses of Lomotil, the following other adverse reactions have been reported; they are listed in decreasing order of severity, but not of frequency:

Nervous system: numbness of extremities, euphoria, depression, malaise/lethargy, confusion, sedation/drowsiness, dizziness, restlessness, headache, hallucination

Allergic: anaphylaxis, angioneurotic edema, urticaria, swelling of the gums, pruritus

Gastrointestinal system: megacolon, paralytic ileus, pancreatitis, vomiting, nausea, anorexia, abdominal discomfort

The following adverse reactions related to atropine sulfate are listed in decreasing order of severity, but not of frequency: hyperthermia, tachycardia, urinary retention, flushing, dryness of the skin and mucous membranes.

DRUG ABUSE AND DEPENDENCE

Controlled substance

Lomotil is classified as a Schedule V controlled substance by federal regulation. Diphenoxylate hydrochloride is chemically related to the narcotic analgesic meperidine.

Drug abuse and dependence

DEPENDENCE

In doses used for the treatment of diarrhea, whether acute or chronic, diphenoxylate has not produced addiction.

Diphenoxylate hydrochloride is devoid of morphine-like subjective effects at therapeutic doses. At high doses it exhibits codeine-like subjective effects. The dose which produces antidiarrheal action is widely separated from the dose which causes central nervous system effects. The insolubility of diphenoxylate hydrochloride in commonly available aqueous media precludes intravenous self-administration. A dose of 100 to 300 mg/day, which is equivalent to 40 to 120 tablets, administered to humans for 40 to 70 days, produced opiate withdrawal symptoms. Since addiction to diphenoxylate hydrochloride is possible at high doses, the recommended dosage should not be exceeded.

OVERDOSAGE

Diagnosis

Overdosage can be life-threatening. Symptoms of overdosage may include opioid and/or anticholinergic effects including respiratory depression, coma, delirium, lethargy, dryness of the skin and mucous membranes, mydriasis or miosis, flushing, hyperthermia, tachycardia, hypotonia, tachypnea, toxic encephalopathy, seizures and incoherent speech.

Respiratory depression has been reported up to 30 hours after ingestion and may recur despite an initial response to narcotic antagonists.

Treat all possible Lomotil overdosages as serious and maintain medical observation/hospitalization until patients become asymptomatic without naloxone use.

Treatment

A pure narcotic antagonist (e.g., naloxone) should be used in the treatment of respiratory depression caused by Lomotil. Refer to the prescribing information for naloxone. Consider Lomotil toxicity even in settings of negative toxicology tests.

Following initial improvement of respiratory function, repeated doses of naloxone hydrochloride may be required to counteract recurrent respiratory depression.

If over-exposure occurs, call your Poison Control Center at 1-800-222-1222 for current information on the management of poisoning or overdosage.

DOSAGE AND ADMINISTRATION

Management of Diarrhea in Patients 13 Years of Age and Older

Lomotil is recommended as adjunctive therapy for the management of diarrhea in patients 13 years of age and older. Consider the nutritional status and degree of dehydration in patients prior to initiating therapy with Lomotil. The use of Lomotil should be accompanied by appropriate fluid and electrolyte therapy, when indicated. If severe dehydration or electrolyte imbalance is present, do not administer Lomotil until appropriate corrective therapy has been indicated (see WARNINGS).

Initial and Maximum Recommended Dosage in Patients 13 Years of Age and Older

The initial adult dosage is 2 Lomotil tablets four times daily (maximum total daily dose of 20 mg per day of diphenoxylate hydrochloride). Most patients will require this dosage until initial control of diarrhea has been achieved. Clinical improvement of acute diarrhea is usually observed within 48 hours.

Dosage after Initial Control of Diarrhea

After initial control has been achieved, the Lomotil dosage may be reduced to meet individual requirements. Control may often be maintained with as little as two Lomotil tablets daily.

Duration of Treatment

If clinical improvement of chronic diarrhea after treatment with the maximum recommended daily dosage is not observed within 10 days, discontinue Lomotil as symptoms are unlikely to be controlled by further administration.

HOW SUPPLIED

Tablets — round, white, with SEARLE debossed on one side and 61 on the other side and containing 2.5 mg of diphenoxylate hydrochloride and 0.025 mg of atropine sulfate, supplied as:

NDC Number | Size
0025-0061-31 | bottle of 100

STORAGE AND HANDLING

Store below 25°C (77°F).

This product's labeling may have been updated. For the most recent prescribing information, please visit www.pfizer.com.

LAB-0065-7.0
Revised March 2025

PRINCIPAL DISPLAY PANEL - 2.5 mg/0.025 mg Tablet Bottle Label

Pfizer

NDC 0025-0061-31

Lomotil®
CV

(diphenoxylate
hydrochloride and
atropine sulfate) tablets, USP

2.5 mg/0.025 mg*

100 Tablets
Rx only